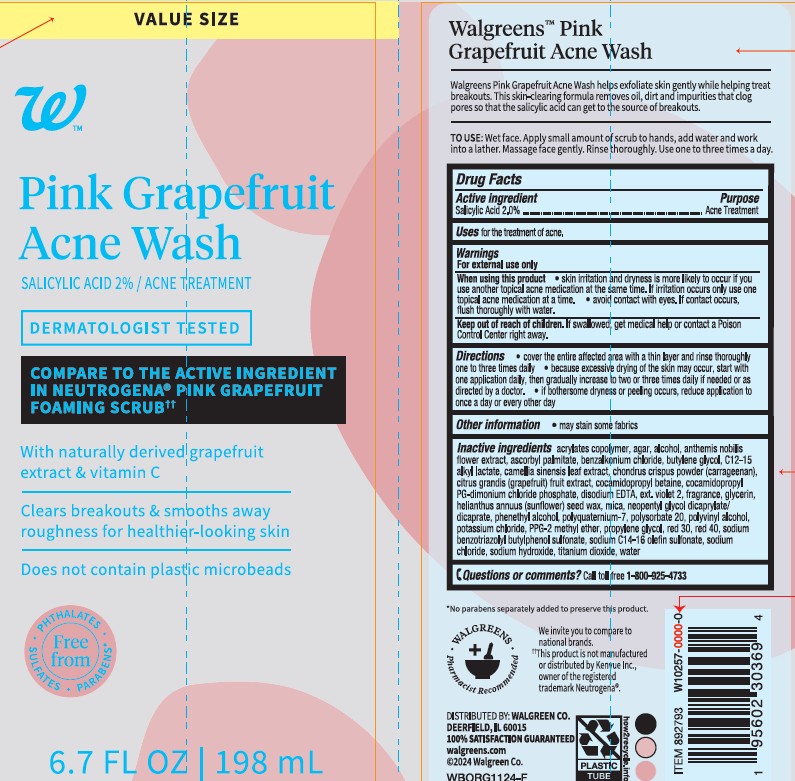 DRUG LABEL: Walgreens Pink Grapefruit Acne Wash
NDC: 0363-0406 | Form: LOTION
Manufacturer: WALGREEN COMPANY
Category: otc | Type: HUMAN OTC DRUG LABEL
Date: 20250320

ACTIVE INGREDIENTS: SALICYLIC ACID 20 mg/1 mL
INACTIVE INGREDIENTS: METHACRYLIC ACID - ETHYL ACRYLATE COPOLYMER (4500 MPA.S); HELIANTHUS ANNUUS SEED WAX; C12-15 ALKYL LACTATE; POLYQUATERNIUM-7 (70/30 ACRYLAMIDE/DADMAC; 1600 KD); PUMMELO; SODIUM C14-16 OLEFIN SULFONATE; SODIUM HYDROXIDE; D&C VIOLET NO. 2; EDETATE DISODIUM; BUTYLENE GLYCOL; CHAMAEMELUM NOBILE FLOWER; FD&C RED NO. 40; NEOPENTYL GLYCOL DICAPRYLATE/DICAPRATE; SODIUM BENZOTRIAZOLYL BUTYLPHENOL SULFONATE; POLYVINYL ALCOHOL, UNSPECIFIED; ASCORBYL PALMITATE; D&C RED NO. 30; SODIUM CHLORIDE; PROPYLENE GLYCOL; CHONDRUS CRISPUS; TITANIUM DIOXIDE; WATER; COCAMIDOPROPYL BETAINE; GLYCERIN; COCAMIDOPROPYL PG-DIMONIUM CHLORIDE PHOSPHATE; POLYSORBATE 20; BENZALKONIUM CHLORIDE; AGAR; MICA; POTASSIUM CHLORIDE; GREEN TEA LEAF

Walgreens Pink Grapefruit Acne Wash

Active ingredients

Salicylic acid 2.0%

Purpose

Acne Treatment

Uses

For the treatment of acne.

Warnings

For external use only

When using this product

• skin irritation and dryness is more likely to occur if you use another topical acne medication at the same time. If irritation occurs, only use one topical acne medication at a time. • avoid contact with eyes. If contact occurs, flush thoroughly with water.

Keep out of reach of children.

If swallowed, get medical help or contact a Poison Control Center right away.

Directions

• cover the entire affected area with a thin layer and rinse thoroughly one to three times daily

• because excessive drying of the skin may occur, start with one application daily, then gradually increase to two or three times daily if needed or as directed by a doctor.

• if bothersome dryness or peeling occurs, reduce application to once a day or every other day

Other Information

• may stain some fabrics

Inactive ingredients

Water, Sodium C14-16 Olefin Sulfonate, Glycerin, Cocamidopropyl Betaine, Helianthus Annuus (Sunflower) Seed Wax, Acrylates Copolymer, Chondrus Crispus Powder (Carrageenan), C12-15 Alkyl Lactate, Disodium EDTA, Cocamidopropyl PG-Dimonium Chloride Phosphate, Citrus Grandis (Grapefruit) Fruit Extract, Polyquaternium-7, Camellia Sinensis Leaf Extract, Ascorbyl Palmitate, Neopentyl Glycol Dicaprylate/ Dicaprate, Anthemis Nobilis Flower Extract, Polysorbate 20, Polyvinyl Alcohol, Propylene Glycol, Sodium Chloride, Benzalkonium Chloride, Butylene Glycol, Sodium Benzotriazolyl Butylphenol Sulfonate, Agar, Fragrance, Sodium Hydroxide, Potassium Chloride, Mica, Titanium Dioxide, Red 30, Red 40, Ext. Violet 2